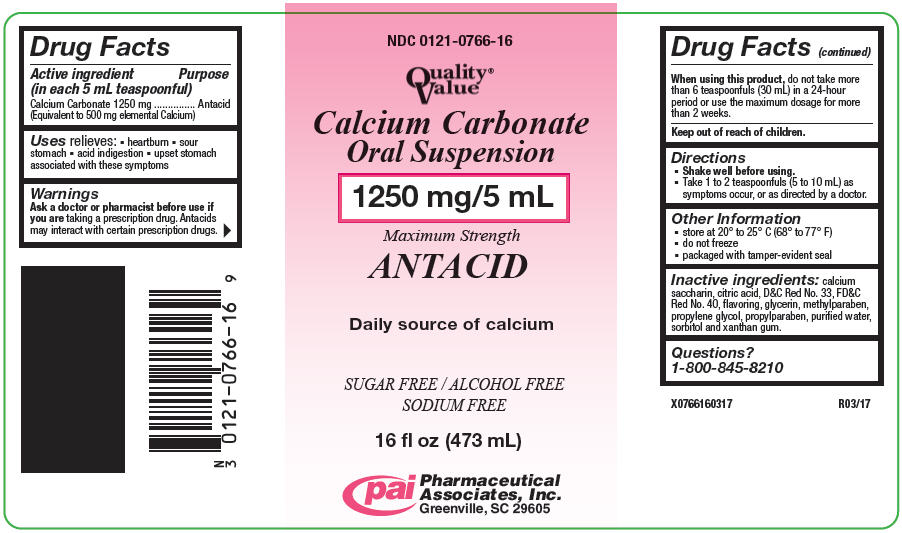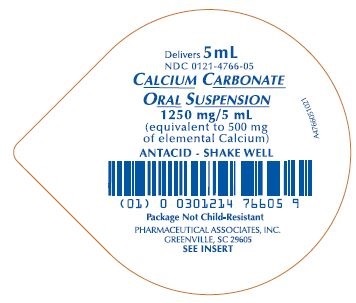 DRUG LABEL: Calcium Carbonate
NDC: 0121-0766 | Form: SUSPENSION
Manufacturer: PAI Holdings, LLC dba PAI Pharma
Category: otc | Type: HUMAN OTC DRUG LABEL
Date: 20241112

ACTIVE INGREDIENTS: CALCIUM CARBONATE 1250 mg/5 mL
INACTIVE INGREDIENTS: D&C RED NO. 33; SACCHARIN CALCIUM; WATER; PROPYLPARABEN; METHYLPARABEN; PROPYLENE GLYCOL; SORBITOL; GLYCERIN; XANTHAN GUM; ANHYDROUS CITRIC ACID; FD&C RED NO. 40

Calcium Carbonate

Drug Facts

Active ingredient (in each 5 mL teaspoonful)

Calcium Carbonate 1250 mg
(Equivalent to 500 mg elemental Calcium)

Purpose

Antacid

Uses

Relieves:

- heartburn
- acid indigestion
- sour stomach
- upset stomach associated with these symptoms

Warnings

Ask a doctor or pharmacist before use if you are taking a prescription drug. Antacids may interact with certain prescription drugs.

When using this product, do not take more than 6 teaspoonfuls (30 mL) in a 24-hour period or use the maximum dosage for more than 2 weeks.

Keep out of reach of children.

Directions

- Shake well before using.
- Take 1 to 2 teaspoonfuls (5 to 10 mL) as symptoms occur, or as directed by a doctor.

Other information

- store at 20° - 25°C (68° - 77°F)
- do not freeze
- Calcium Carbonate Oral Suspension is a pink-colored, bubble gum flavored suspension supplied in the following oral dosage forms:

NDC 0121-0766-16: | 16 fl oz (473 mL) bottle
NDC 0121-4766-05: | 5 mL unit dose cup, in a tray of ten cups.

Inactive ingredients

calcium saccharin, citric acid, D&C Red No. 33, FD&C Red No. 40, flavoring, glycerin, methylparaben, propylene glycol, propylparaben, purified water, sorbitol and xanthan gum.

Questions or comments?

Call 1-800-845-8210.

You may also report serious side effects to this phone number.

MANUFACTURED BY

Pharmaceutical Associates, Inc. Greenville, SC 29605

R07/20

PRINCIPAL DISPLAY PANEL - 473 mL Bottle Label

NDC 0121-0766-16

Quality®
Value

Calcium Carbonate
Oral Suspension

1250 mg/5 mL

Maximum Strength
ANTACID

Daily source of calcium

SUGAR FREE / ALCOHOL FREE
SODIUM FREE

16 fl oz (473 mL)

Pharmaceutical
Associates, Inc.
Greenville, SC 29605

PRINCIPAL DISPLAY PANEL - 5 mL Cup Tray Label

Delivers 5 mL

NDC 0121-4766-05

Calcium Carbonate Oral Suspension
1250 mg/5 mL

(equivalent to 500 mg of elemental Calcium)

ANTACID – SHAKE WELL

Package Not Child-Reistant

Pharmaceutical Associates, Inc.

Greenville, SC 29605

SEE INSERT

A0766051021